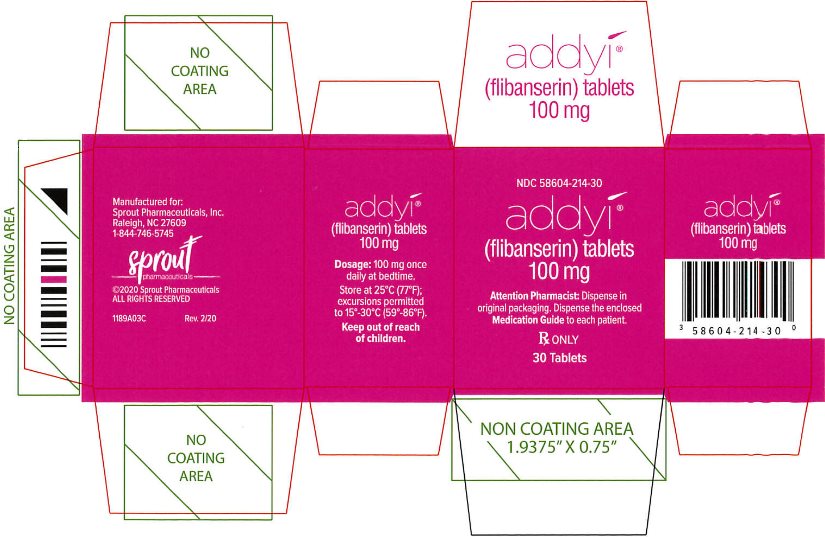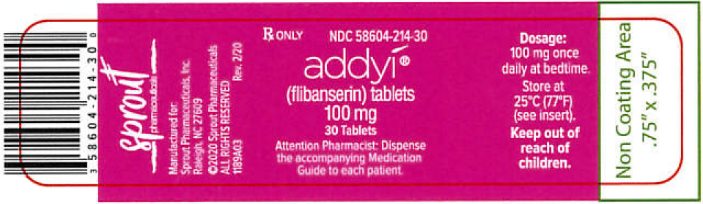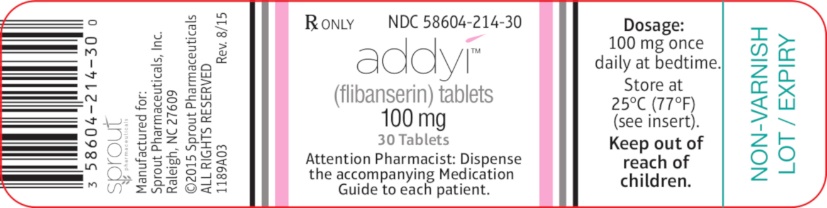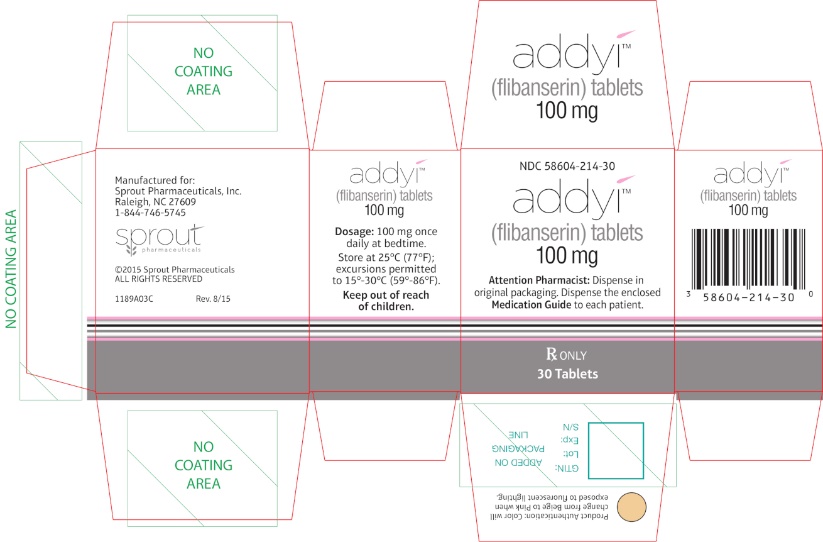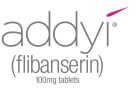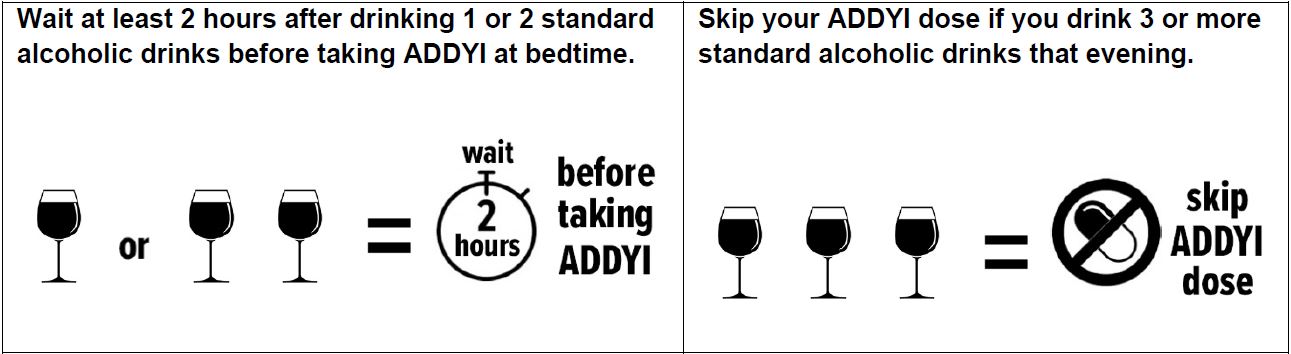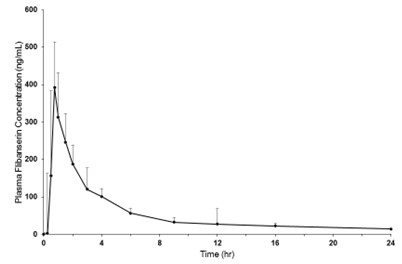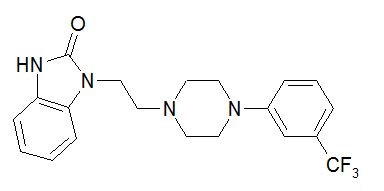 DRUG LABEL: ADDYI
NDC: 58604-214 | Form: TABLET, FILM COATED
Manufacturer: Sprout Pharmaceuticals, Inc.
Category: prescription | Type: HUMAN PRESCRIPTION DRUG LABEL
Date: 20251222

ACTIVE INGREDIENTS: Flibanserin 100 mg/1 1
INACTIVE INGREDIENTS: Lactose Monohydrate; Microcrystalline Cellulose; Hypromellose, Unspecified; Croscarmellose Sodium; Magnesium Stearate; Talc; Polyethylene Glycol, Unspecified; Titanium Dioxide; Ferric Oxide Red

HIGHLIGHTS OF PRESCRIBING INFORMATION

These highlights do not include all the information needed to use ADDYI safely and effectively.
See full prescribing information for ADDYI.
ADDYI (flibanserin) tablets, for oral use
Initial U.S. Approval: 2015

RECENT MAJOR CHANGES SECTION

Indications and Usage (1) | 12/2025

WARNING: HYPOTENSION and SYNCOPE IN CERTAIN SETTINGS

See full prescribing information for complete boxed warning.

- Use of ADDYI and alcohol together close in time increases the risk of severe hypotension and syncope. Counsel patients to wait at least two hours after consuming one or two standard alcoholic drinks before taking ADDYI at bedtime or to skip their ADDYI dose if they have consumed three or more standard alcoholic drinks that evening. (4, 5.1)
- Severe hypotension and syncope can occur when ADDYI is used with moderate or strong CYP3A4 inhibitors or in patients with hepatic impairment; therefore, ADDYI use in these settings is contraindicated. (4, 5.2, 5.5)

1 INDICATIONS AND USAGE

ADDYI is indicated for the treatment of women less than 65 years of age with acquired, generalized hypoactive sexual desire disorder (HSDD) as characterized by low sexual desire that causes marked distress or interpersonal difficulty and is not due to (1):

- A co-existing medical or psychiatric condition,
- Problems within the relationship, or
- The effects of a medication or other drug substance.

Limitations of Use:

- ADDYI is not indicated in men (1)
- ADDYI is not indicated to enhance sexual performance. (1)

2 DOSAGE AND ADMINISTRATION

- Recommended dosage is 100 mg taken once daily at bedtime (2.1)
- ADDYI is dosed at bedtime because administration during waking hours increases risks of hypotension, syncope, accidental injury, and central nervous system (CNS) depression (2.1)
- Discontinue ADDYI treatment after 8 weeks if no improvement (2.3)

3 DOSAGE FORMS AND STRENGTHS

Tablets: 100 mg (3)

4 CONTRAINDICATIONS

- Moderate or strong cytochrome P450 3A4 (CYP3A4) inhibitors (4, 5.2)
- Hepatic impairment (4, 5.5)
- Known hypersensitivity to ADDYI or its components (4, 5.6, 6.2)

5 WARNINGS AND PRECAUTIONS

- Hypotension and Syncope due to an Interaction with Alcohol: After taking ADDYI at bedtime, advise patients to avoid alcohol until the following day. (5.1)
- Central Nervous System (CNS) Depression (e.g., Somnolence, Sedation): Can occur with ADDYI alone. Exacerbated by other CNS depressants, and in settings where flibanserin concentrations are increased. Patients should avoid activities requiring full alertness (e.g., driving or operating machinery) until at least six hours after each dose and until they know how ADDYI affects them. (5.3)
- Hypotension and Syncope with ADDYI Alone: Patients with pre-syncope should immediately lie supine and promptly seek medical help if symptoms do not resolve. (5.4)
- Hypersensitivity Reactions, including anaphylaxis, angioedema, pruritus, urticaria: Avoid in women with known hypersensitivity to ADDYI or any of its components (5.6)

6 ADVERSE REACTIONS

Most common adverse reactions (incidence ≥2%) are dizziness, somnolence, nausea, fatigue, insomnia, urinary tract infection, anxiety, sinusitis, constipation and dry mouth. (6.1)

To report SUSPECTED ADVERSE REACTIONS, contact Sprout Pharmaceuticals, Inc. at 1-844-746-5745, or FDA at 1-800-FDA-1088 or www.fda.gov/medwatch.

7 DRUG INTERACTIONS

- Oral Contraceptives and Other Weak CYP3A4 Inhibitors: Increases flibanserin exposures and incidence of adverse reactions (6.1, 7)
- Strong CYP2C19 Inhibitors: Increases flibanserin exposure which may increase risk of hypotension, syncope, and CNS depression (7)
- CYP3A4 Inducers: Use of ADDYI not recommended; flibanserin concentrations substantially reduced (7)
- Digoxin: Increases digoxin concentrations, which may lead to digoxin toxicity. Increase monitoring of digoxin concentrations (7)

8 USE IN SPECIFIC POPULATIONS

- Nursing Mothers: ADDYI is not recommended. (8.2)
- CYP2C19 Poor Metabolizers: Increases flibanserin exposure which may increase risk of hypotension, syncope, and CNS depression (8.7)

FULL PRESCRIBING INFORMATION

WARNING: HYPOTENSION and SYNCOPE IN CERTAIN SETTINGS

Interaction with Alcohol

The use of ADDYI and alcohol together close in time increases the risk of severe hypotension and syncope [see Warnings and Precautions (5.1)]. Counsel patients to wait at least two hours after consuming one or two standard alcoholic drinks before taking ADDYI at bedtime or to skip their ADDYI dose if they have consumed three or more standard alcoholic drinks that evening.

Contraindicated with Strong or Moderate CYP3A4 Inhibitors

The concomitant use of ADDYI and moderate or strong CYP3A4 inhibitors increases flibanserin concentrations, which can cause severe hypotension and syncope [see Warnings and Precautions (5.2)]. Therefore, the use of moderate or strong CYP3A4 inhibitors is contraindicated in patients taking ADDYI [see Contraindications (4)].

Contraindicated in Patients with Hepatic Impairment

The use of ADDYI in patients with hepatic impairment increases flibanserin concentrations, which can cause severe hypotension and syncope [see Warnings and Precautions (5.5)]. Therefore, ADDYI is contraindicated in patients with hepatic impairment [see Contraindications (4)].

1 INDICATIONS AND USAGE

ADDYI is indicated for the treatment of women less than 65 years of age with acquired, generalized hypoactive sexual desire disorder (HSDD) as characterized by low sexual desire that causes marked distress or interpersonal difficulty and is not due to:

- A co-existing medical or psychiatric condition,
- Problems within the relationship, or
- The effects of a medication or other drug substance.

Acquired HSDD refers to HSDD that develops in a patient who previously had no problems with sexual desire. Generalized HSDD refers to HSDD that occurs regardless of the type of stimulation, situation or partner.

Limitations of Use

- ADDYI is not indicated in men.
- ADDYI is not indicated to enhance sexual performance.

2 DOSAGE AND ADMINISTRATION

2.1 Recommended Dosage

The recommended dosage of ADDYI is 100 mg administered orally once per day at bedtime. ADDYI is dosed at bedtime because administration during waking hours increases the risks of hypotension, syncope, accidental injury, and central nervous system (CNS) depression (such as somnolence and sedation).

2.2 Missed Dose

If a dose of ADDYI is missed at bedtime, instruct the patient to take the next dose at bedtime on the next day. Instruct the patient to not double the next dose.

2.3 Discontinuation of ADDYI

Discontinue ADDYI after 8 weeks if the patient does not report an improvement in her HSDD symptoms.

2.4 Initiation of ADDYI Following Moderate or Strong CYP3A4 Inhibitor Use

If initiating ADDYI following moderate or strong CYP3A4 inhibitor use, start ADDYI 2 weeks after the last dose of the CYP3A4 inhibitor.

If initiating a moderate or strong CYP3A4 inhibitor following ADDYI use, start the moderate or strong CYP3A4 inhibitor 2 days after the last dose of ADDYI [see Warnings and Precautions (5.2)].

3 DOSAGE FORMS AND STRENGTHS

Tablets: 100 mg, oval, pink, debossed on one side with "f100" and blank on the other side.

4 CONTRAINDICATIONS

ADDYI is contraindicated in patients:

- Using concomitant moderate or strong CYP3A4 inhibitors [see Boxed Warning and Warnings and Precautions (5.2)].
- With hepatic impairment [see Boxed Warning and Warnings and Precautions (5.5)].
- With known hypersensitivity to ADDYI or any of its components. Reactions, including anaphylaxis, reactions consistent with angioedema (e.g., swelling of the face, lips, and mouth), pruritus, and urticaria have been reported [see Adverse Reactions (6.2)].

5 WARNINGS AND PRECAUTIONS

5.1 Hypotension and Syncope due to an Interaction with Alcohol

Taking ADDYI within two hours after consuming alcohol increases the risk of severe hypotension and syncope. To reduce this risk, counsel patients to wait at least two hours after drinking one or two standard alcoholic drinks before taking ADDYI at bedtime [see Boxed Warning and Adverse Reactions (6.1)]. Patients who drink three or more standard alcoholic drinks should skip their ADDYI dose that evening. One standard alcoholic drink contains 14 grams of pure alcohol and is equivalent to one 12-ounce regular beer (5% alcohol), 5-ounces wine (12% alcohol), or 1.5 ounces of distilled spirits/shot (40% alcohol).

After taking ADDYI at bedtime, advise patients to not use alcohol until the following day.

5.2 Hypotension and Syncope with CYP3A4 Inhibitors

Moderate or Strong CYP3A4 Inhibitors

The concomitant use of ADDYI with moderate or strong CYP3A4 inhibitors significantly increases flibanserin concentrations, which can lead to hypotension and syncope [see Adverse Reactions (6.1)]. The concomitant use of ADDYI with a moderate or strong CYP3A4 inhibitor is contraindicated. If the patient requires a moderate or strong CYP3A4 inhibitor, discontinue ADDYI at least 2 days prior to starting the moderate or strong CYP3A4 inhibitor. In cases where the benefit of initiating a moderate or strong CYP3A4 inhibitor within 2 days of stopping ADDYI clearly outweighs the risk of flibanserin exposure related hypotension and syncope, monitor the patient for signs of hypotension and syncope. Discontinue the moderate or strong CYP3A4 inhibitor for 2 weeks before restarting ADDYI [see Drug Interactions (7)].

Multiple Concomitant Weak CYP3A4 Inhibitors
Concomitant use of multiple weak CYP3A4 inhibitors that may include herbal supplements (e.g., ginkgo, resveratrol) or non-prescription drugs (e.g., cimetidine) could also lead to clinically relevant increases in flibanserin concentrations that may increase the risk of hypotension and syncope [see Drug Interactions (7)].

5.3 Central Nervous System Depression

ADDYI can cause CNS depression (e.g., somnolence, sedation). In five 24-week, randomized, placebo-controlled, double-blind trials of premenopausal women with HSDD, the incidence of somnolence, sedation or fatigue was 21% and 8% in patients treated with 100 mg ADDYI once daily at bedtime and placebo, respectively [see Adverse Reactions (6.1) and Clinical Studies (14.1)]. In two similarly designed trials in naturally postmenopausal women with acquired, generalized HSDD, the incidence of somnolence, sedation or fatigue was 10% and 6% in patients less than 65 years of age treated with 100 mg ADDYI once daily at bedtime and placebo, respectively. The risk of CNS depression is increased if ADDYI is taken during waking hours, or if ADDYI is taken with alcohol or other CNS depressants, or with medications that increase flibanserin concentrations, such as CYP3A4 inhibitors [see Contraindications (4), Warnings and Precautions (5.1, 5.2), Adverse Reactions (6.1), and Drug Interactions (7)].

Patients should avoid activities requiring full alertness (e.g., driving or operating machinery) until at least 6 hours after taking ADDYI and until they know how ADDYI affects them [see Clinical Studies (14.3)].

5.4 Hypotension and Syncope with ADDYI Alone

The use of ADDYI − without other concomitant medications known to cause hypotension or syncope − can cause hypotension and syncope. In five 24-week, randomized, placebo-controlled, double-blind trials of premenopausal women with HSDD, hypotension was reported in 0.2% and <0.1% of ADDYI-treated patients and placebo-treated patients, respectively; syncope was reported in 0.4% and 0.2% of ADDYI‑treated patients and placebo-treated patients, respectively. In two similarly designed trials in naturally postmenopausal women with acquired, generalized HSDD, there was no difference in the incidence of hypotension between ADDYI-treated patients and placebo-treated patients. One case of syncope was reported in the ADDYI treatment group.

The risk of hypotension and syncope is increased if ADDYI is taken during waking hours or if higher than the recommended dose is taken [see Warnings and Precautions (5.1, 5.3), Adverse Reactions (6.1), Drug Interactions (7), and Use in Specific Populations (8.7)].

Consider the benefits of ADDYI and the risks of hypotension and syncope in patients with pre-existing conditions that predispose to hypotension. Patients who experience pre-syncope should immediately lie supine and promptly seek medical help if the symptoms do not resolve. Prompt medical attention should also be obtained for patients who experience syncope.

5.5 Syncope and Hypotension in Patients with Hepatic Impairment

The use of ADDYI in patients with any degree of hepatic impairment significantly increases flibanserin concentrations, which can lead to hypotension and syncope. Therefore, the use of ADDYI is contraindicated in patients with hepatic impairment [see Contraindications (4), Use in Specific Populations (8.6) and Clinical Pharmacology (12.3)].

5.6 Hypersensitivity Reactions

Hypersensitivity reactions, including anaphylaxis, reactions consistent with angioedema (e.g., swelling of the face, lips, and mouth), pruritus, and urticaria have been reported with ADDYI. ADDYI is contraindicated in women with known hypersensitivity to ADDYI or any of its components [see Adverse Reactions (6.2)]. Immediately discontinue ADDYI and initiate appropriate treatment if a hypersensitivity reaction occurs.

5.7 Mammary Tumors in Female Mice

In a 2-year carcinogenicity study in mice, there was a statistically significant and dose-related increase in the incidence of malignant mammary tumors in female mice at flibanserin exposures 3 and 10 times the recommended clinical dose of ADDYI. No such increases were seen in male mice or in male or female rats [see Nonclinical Toxicology (13.1)]. The clinical significance of these findings is unknown.

6 ADVERSE REACTIONS

The following adverse reactions are discussed in greater detail in other sections of the labeling:

- Hypotension and syncope [see Warnings and Precautions (5.1, 5.2, 5.4, 5.5)]
- CNS depression [see Warnings and Precautions (5.3)]

6.1 Clinical Trials Experience

Because clinical trials are conducted under widely varying conditions, adverse reaction rates observed in the clinical trials of a drug cannot be directly compared to the rates in the clinical trials of another drug and may not reflect the rates observed in practice.

The approved 100 mg ADDYI dosage at bedtime was administered to 2,997 premenopausal women with acquired, generalized HSDD in clinical trials, of whom 1,672 received treatment for at least 6 months, 850 received treatment for at least 12 months, and 88 received treatment for at least 18 months [see Clinical Studies (14)].

In clinical trials, ADDYI 100 mg once daily at bedtime was administered to 801 postmenopausal women less than 65 years of age with acquired, generalized HSDD, of whom 460 received ADDYI treatment for at least 6 months, and 23 received ADDYI treatment for longer than 6 months.

Premenopausal Women

The data presented below in Table 1 and Table 2 (left columns) are derived from five 24-week randomized, double-blind, placebo-controlled trials in premenopausal women with acquired, generalized HSDD. In these trials, the frequency and quantity of alcohol use was not recorded. Three of these trials (Studies 1, 2, and 3) also provided efficacy data [see Clinical Studies (14.1)]. One trial (Study 5) did not evaluate the 100 mg bedtime dose.

In four trials in premenopausal women (Studies 1 through 4), 100 mg ADDYI at bedtime was administered to 1543 premenopausal women with HSDD, of whom 1060 completed 24 weeks of treatment. The age range of women enrolled was 18-56 years old with a mean age of 36 years old, and 88% were Caucasian and 9% were Black.

In Studies 1 through 4 in premenopausal women, serious adverse reactions were reported in 0.9% and 0.5% of ADDYI-treated patients and placebo-treated patients, respectively.

Postmenopausal Women

The data presented below in Table 1 and Table 2 (right columns) are derived from two randomized, double-blind, placebo-controlled trials intended to be of 24-week duration in naturally postmenopausal women with acquired, generalized HSDD (Studies 6 and 7). One trial (Study 7) was discontinued prematurely. In these trials, 100 mg ADDYI at bedtime was administered to 801 postmenopausal women less than 65 years of age with HSDD, of whom 460 completed 24 weeks of treatment. The age range of women enrolled was 34-80 years old with a mean age of 56 years old, and 91% were Caucasian, 7% were Black and 94% were less than 65 years of age. The clinical trial population had no significant comorbid medical conditions and were not taking concomitant medications. Serious adverse reactions were reported in 1.5% and 0.7% of ADDYI-treated patients and placebo-treated patients less than 65 years of age, respectively.

Adverse Reactions Leading to Discontinuation
Table 1 displays the most common adverse reactions leading to discontinuation in six trials of women less than 65 years of age with HSDD that evaluated the ADDYI 100 mg once daily at bedtime dosage by population studied.

Table 1 Adverse Reactions [Adverse reactions leading to discontinuation of >1% of patients who received ADDYI 100 mg once daily at bedtime and at a higher incidence than placebo-treated patients in the pooled premenopausal women and postmenopausal women trials.] Leading to Discontinuation in Randomized, Double-blind, Placebo-controlled Trials in Women with HSDD (< 65 Years of Age)
Adverse Reaction | Trials in Premenopausal Women [Includes Studies 1-4] |  | Trials in Postmenopausal Women [Includes Studies 6 and 7]
Adverse Reaction | Placebo (N=1556) | ADDYI (N=1543) | Placebo (N=797) | ADDYI (N=801)
Overall | 6% | 13% | 5% | 9%
Dizziness | 0.1% | 1.7% | 0.3% | 0.9%
Nausea | 0.1% | 1.2% | 0.3% | 0.5%
Insomnia | 0.2% | 1.1% | 0.5% | 1.4%
Somnolence | 0.3% | 1.1% | 0.1% | 0.6%
Anxiety | 0.3% | 1% | 0.6% | 1.2%

Most Common Adverse Reactions
Table 2 summarizes the most common adverse reactions reported in six trials of women less than 65 years of age with HSDD. This table shows adverse reactions reported in at least 2% of patients treated with ADDYI and at a higher incidence than with placebo [see Warnings and Precautions (5.3)]. The majority of these adverse reactions began within the first 14 days of treatment.

Table 2 Common Adverse Reactions [Adverse reactions reported in ≥2% of patients who received ADDYI 100 mg once daily at bedtime and at a higher incidence than placebo-treated patients in premenopausal women or postmenopausal women trials.] in Randomized, Double-blind, Placebo-controlled Trials in Women with HSDD (<65 Years of Age)
 | Trials in Premenopausal Women |  | Trials in Postmenopausal Women
Adverse Reaction | Placebo (N=1556) | ADDYI (N=1543) | Placebo (N=797) | ADDYI (N=801)
Dizziness | 2.2% | 11.4% | 3.3% | 7.9%
Somnolence | 2.9% | 11.2% | 1.8% | 7.7%
Nausea | 3.9% | 10.4% | 3.9% | 6.6%
Fatigue | 5.5% | 9.2% | 3.9% | 3.0%
Insomnia | 2.8% | 4.9% | 3.4% | 5.7%
Dry mouth | 1.0% | 2.4% | 1.3% | 2.4%
Urinary tract infection | 2.4% | 2.3% | 3.0% | 3.2%
Anxiety | 1.0% | 1.8% | 1.6% | 2.6%
Sinusitis | 3.5% | 2.9% | 2.1% | 2.5%
Constipation | 0.4% | 1.6% | 1.8% | 2.5%

Less Common Adverse Reactions
In six trials in women less than 65 years of age with HSDD treated with ADDYI 100 mg once daily at bedtime, less common adverse reactions (reported in ≥1% but <2% of ADDYI-treated patients and at a higher incidence than with placebo) in the premenopausal population included: abdominal pain, metrorrhagia, rash, sedation, vertigo. In the postmenopausal population, less common adverse reactions included: sleep disorder, bronchitis, edema peripheral, cough, vertigo, palpitations, rash, abnormal dreams.

Appendicitis
In the five trials of premenopausal women with HSDD, appendicitis was reported in 6/3973 (0.2%) flibanserin-treated patients, while there were no reports of appendicitis in the 1905 placebo-treated patients. Appendicitis was not reported in trials of postmenopausal women.

Accidental Injury
In five trials of premenopausal women with HSDD, accidental injury was reported in 42/1543 (2.7%) ADDYI-treated patients and 47/1905 (2.5%) placebo-treated patients. Among these 89 patients who experienced injuries, 9/42 (21%) ADDYI-treated patients and 3/47 (6%) placebo-treated patients reported adverse reactions consistent with CNS depression (e.g., somnolence, fatigue, or sedation) within the preceding day. In two trials of postmenopausal women less than 65 years of age with HSDD, accidental injury was reported in 33/801 (4.1%) ADDYI-treated patients and 28/797 (3.5%) placebo-treated patients. Among these 61 patients who experienced injuries, 1/33 (3.0%) ADDYI-treated patients and 3/28 (10.7%) placebo-treated patients reported adverse reactions consistent with CNS depression (e.g., somnolence, fatigue, or sedation) the preceding day.

Adverse Reactions in Patients Who Reported Hormonal Contraceptive Use
In four trials of premenopausal women with HSDD, 1466 patients (43%) reported concomitant use of hormonal contraceptives (HC) at study enrollment. These trials were not prospectively designed to assess an interaction between ADDYI and HC. ADDYI-treated patients who reported HC use had a greater incidence of dizziness, somnolence, and fatigue compared to ADDYI-treated patients who did not report HC use (dizziness 9.9% in HC non-users, 13.4% in HC users; somnolence 10.6% in HC non-users, 12.3% in HC users; fatigue 7.5% in HC non-users, 11.4% in HC users). There were no meaningful differences in the incidence of these adverse reactions in placebo-treated patients who reported or did not report HC use [see Drug Interactions (7)].

Data from Other Trials
One death occurred in a 54 year-old postmenopausal woman treated with 100 mg ADDYI taken at bedtime. This patient had a history of hypertension and hypercholesterolemia and baseline alcohol consumption of 1-3 drinks daily. She died of acute alcohol intoxication 14 days after starting ADDYI. Blood alcohol concentration on autopsy was 0.289 g/dL. The autopsy report also noted coronary artery disease. A relationship between this patient’s death and use of ADDYI is unknown [see Boxed Warning and Warnings and Precautions (5.1)].

Hypotension, Syncope, and CNS Depression in Studies of Healthy Subjects

Hypotension, Syncope, and CNS Depression with Alcohol

Alcohol and ADDYI Administration at the Same Time
The first alcohol interaction study was conducted in 25 healthy subjects (23 men and 2 premenopausal women). The study excluded subjects who drank fewer than five alcoholic drinks per week and those with a history of orthostatic hypotension, or syncope. A single dose of 100 mg ADDYI was administered concurrently with 0.4 g/kg or 0.8 g/kg alcohol in the morning; alcohol was consumed over 10 minutes. Hypotension or syncope requiring therapeutic intervention (ammonia salts and/or placement in supine or Trendelenburg position) occurred in 4 (17%) of the 23 subjects co-administered 100 mg ADDYI and 0.4 g/kg alcohol (equivalent to two 12 ounce cans of beer containing 5% alcohol content, two 5 ounce glasses of wine containing 12% alcohol content, or two 1.5 ounce shots of 80-proof spirit in a 70 kg person). In these four subjects, all of whom were men, the magnitude of the systolic blood pressure reductions ranged from 28 to 54 mmHg and the magnitude of the diastolic blood pressure reductions ranged from 24 to 46 mmHg. In addition, 6 (25%) of the 24 subjects co-administered 100 mg ADDYI and 0.8 g/kg alcohol (equivalent to four 12 ounce cans of beer containing 5% alcohol content, four 5 ounce glasses of wine containing 12% alcohol content, or four 1.5 ounce shots of 80-proof spirit in a 70 kg person) experienced orthostatic hypotension when standing from a sitting position. The magnitude of the systolic blood pressure reduction in these 6 subjects ranged from 22 to 48 mmHg, and the diastolic blood pressure reductions ranged from 0 to 27 mmHg. One of these subjects required therapeutic intervention (ammonia salts and placement supine with the foot of the bed elevated). There were no events requiring therapeutic interventions when ADDYI or alcohol were administered alone.

In this study, somnolence was reported in 67%, 74%, and 92% of subjects who received ADDYI alone, ADDYI in combination with 0.4 g/kg alcohol, and ADDYI in combination with 0.8 g/kg alcohol, respectively. [see Boxed Warning, Warnings and Precautions (5.1, 5.3 and 5.4)].

In the second alcohol interaction study, 96 healthy premenopausal women received a single dose of 100 mg ADDYI concurrently with 0.2 g/kg, 0.4 g/kg, or 0.6 g/kg alcohol (equivalent to one, two or three alcoholic drinks in a 70 kg person, respectively) in the morning. The study excluded subjects with a history of syncope, orthostatic hypotension, hypotensive events, and dizziness, and those with a resting systolic blood pressure less than 110 mmHg or diastolic blood pressure less than 60 mmHg.

In this study, no subjects experienced syncope or hypotension requiring therapeutic intervention. However, subjects who were already hypotensive (blood pressure below 90/60 mmHg) or symptomatic (e.g., dizzy) while in the semi-recumbent position were not permitted to stand for orthostatic measurements, and those with blood pressures below 90/40 mmHg while in the semi-recumbent position had blood pressures repeated until it was deemed safe for them to change position. More subjects had missing or delayed orthostatic measurements (in general, due to hypotension or dizziness) when receiving ADDYI and alcohol, compared to those who received alcohol alone or ADDYI alone. This pattern of missing or delayed orthostatic measurements is concerning for a risk of hypotension and syncope if those subjects had been allowed to stand.

In this study, somnolence was reported in 81-89% of subjects administered ADDYI with alcohol, compared to 25-41% of subjects administered alcohol alone and 84% of subjects taking ADDYI alone. Dizziness was reported in 27-40% of subjects administered ADDYI with alcohol, compared to 6-20% of subjects administered alcohol alone and 31% of subjects taking ADDYI alone. [see Warnings and Precautions (5.1, 5.3, 5.4)].

Alcohol Use at Various Time Intervals Before ADDYI Administration
In a third alcohol interaction study, 64 healthy premenopausal women consumed 0.4 g/kg alcohol (equivalent to 2 alcoholic drinks in a 70 kg person) two, four or six hours prior to receiving ADDYI 100 mg or placebo in the afternoon. The study excluded subjects with a history or presence of orthostatic hypotension, history of hypotension, syncope, or dizziness. Prior to receiving alcohol, the subjects in the ADDYI arm had taken ADDYI for three days to achieve steady state. Syncope occurred in one subject who received alcohol alone. The incidences of orthostatic hypotension and hypotension (blood pressure below 90/60 mmHg) at all time points were similar among subjects administered alcohol before ADDYI, subjects administered alcohol alone, and subjects administered ADDYI alone. Three subjects were unable to stand due to feeling dizzy or hypotension; two following alcohol and ADDYI separated by 2 and 6 hours, and one subject who received ADDYI alone.

In this study, somnolence was reported in 35-53% of subjects administered ADDYI and alcohol, compared to 5-8% of subjects taking alcohol alone and 50% of subjects taking ADDYI alone. Dizziness was reported in 5-13% of subjects administered ADDYI and alcohol, compared to 0-3% of subjects taking alcohol alone and 12% of subjects taking ADDYI alone.

Alcohol Use in the Evening Before Bedtime ADDYI Administration
In another alcohol interaction study, 24 premenopausal women consumed 0.4 g/kg alcohol (equivalent to 2 alcoholic drinks in a 70 kg person) during the evening meal two and a half to four hours prior to taking ADDYI 100 mg at bedtime. There were no cases of syncope. Upon rising the following morning, the incidence of hypotension was 23% among subjects administered ADDYI after alcohol, 23% among subjects administered alcohol alone and 36% with ADDYI alone. No cases of somnolence or dizziness were reported in this study. Conclusions are limited because blood pressure and orthostatic measurements were not taken after ADDYI administration until the following morning.

Dedicated alcohol-interaction studies were not conducted in postmenopausal women.

Hypotension and Syncope with Fluconazole
In a pharmacokinetic drug interaction study of 100 mg ADDYI and 200 mg fluconazole (a moderate CYP3A4 inhibitor, moderate CYP2C9 inhibitor, and a strong CYP2C19 inhibitor) in healthy subjects, hypotension or syncope requiring placement supine with legs elevated occurred in 3/15 (20%) subjects treated with concomitant ADDYI and fluconazole compared to no such adverse reactions in subjects treated with ADDYI alone or fluconazole alone. One of these 3 subjects became unresponsive with a blood pressure of 64/41 mm Hg and required transportation to the hospital emergency department where she required intravenous saline. Due to these adverse reactions, the study was stopped. In this study, the concomitant use of ADDYI and fluconazole increased flibanserin exposure 7-fold [see Warnings and Precautions (5.2), Drug Interactions (7) and Clinical Pharmacology (12.3)].

Syncope with Ketoconazole
In a pharmacokinetic drug interaction study of 50 mg flibanserin and 400 mg ketoconazole, a strong CYP3A4 inhibitor, syncope occurred in 1/24 (4%) healthy subjects treated with concomitant flibanserin and ketoconazole, 1/24 (4%) receiving flibanserin alone, and no subjects receiving ketoconazole alone. In this study, the concomitant use of flibanserin and ketoconazole increased flibanserin exposure 4.5-fold [see Warnings and Precautions (5.2), Drug Interactions (7) and Clinical Pharmacology (12.3)].

Syncope in Poor CYP2C19 Metabolizers
In a pharmacogenomic study of 100 mg ADDYI in subjects who were poor or extensive CYP2C19 metabolizers, syncope occurred in 1/9 (11%) subjects who were CYP2C19 poor metabolizers (this subject had a 3.2 fold higher flibanserin exposure compared to CYP2C19 extensive metabolizers) compared to no such adverse reactions in subjects who were CYP2C19 extensive metabolizers [see Drug Interactions (7), Use in Specific Populations (8.7) and Clinical Pharmacology (12.5)].

6.2 Postmarketing Experience

The following adverse reactions have been identified during post-approval use of ADDYI. Because these reactions are reported voluntarily from a population of uncertain size, it is not always possible to reliably estimate their frequency or establish a causal relationship to drug exposure.

- Immune system disorders: hypersensitivity reactions, including anaphylaxis, reactions consistent with angioedema (e.g., swelling of the face, lips, and mouth), pruritus, and urticaria.
- Gastrointestinal disorders: vomiting
- General disorders and administration site conditions: asthenia, feeling abnormal, feeling drunk, malaise
- Nervous system disorders: headache, presyncope, gait disturbance, vision blurred
- Psychiatric disorders: brain fog

7 DRUG INTERACTIONS

Table 3 contains clinically significant drug interactions (DI) with ADDYI.

Table 3 Clinically Significant Drug Interactions with ADDYI
Alcohol
Clinical Implications | The coadministration of ADDYI with alcohol increased the risk of hypotension, syncope, and CNS depression compared to the use of ADDYI alone or alcohol alone [see Warnings and Precautions (5.1) and Clinical Pharmacology (12.2)].
Preventing or Managing DI | Counsel patients to wait at least two hours after consuming one or two standard alcoholic drinks before taking ADDYI at bedtime or to skip their ADDYI dose if they have consumed three or more alcoholic drinks that evening. [see Boxed Warning, Warnings and Precautions (5.1), and Adverse Reactions (6.1)].
Other CNS Depressants
Examples | Diphenhydramine, opioids, hypnotics, benzodiazepines
Clinical Implications | The concomitant use of ADDYI with CNS depressants may increase the risk of CNS depression (e.g., somnolence) compared to the use of ADDYI alone.
Preventing or Managing DI | Discuss the concomitant use of other CNS depressants with the patient when prescribing ADDYI.
Moderate or Strong CYP3A4 Inhibitors
Examples of strong CYP3A4 inhibitors | Ketoconazole, itraconazole, posaconazole, clarithromycin, nefazodone, ritonavir, saquinavir, nelfinavir, indinavir, boceprevir, telaprevir, telithromycin and conivaptan
Examples of moderate CYP3A4 inhibitors | Amprenavir, atazanavir, ciprofloxacin, diltiazem, erythromycin, fluconazole, fosamprenavir, verapamil, and grapefruit juice
Clinical Implications | The concomitant use of ADDYI with moderate or strong CYP3A4 inhibitors increases flibanserin exposure compared to the use of ADDYI alone. The risk of hypotension and syncope is increased with concomitant use of ADDYI and moderate or strong CYP3A4 inhibitors [see Warnings and Precautions (5.2), Adverse Reactions (6.1), and Clinical Pharmacology (12.3)].
Preventing or Managing DI | The concomitant use of ADDYI with moderate or strong CYP3A4 inhibitors is contraindicated.
Weak CYP3A4 Inhibitors
Examples | Oral contraceptives, cimetidine, fluoxetine, ginkgo, ranitidine
Clinical Implications | The concomitant use of ADDYI with multiple weak CYP3A4 inhibitors may increase the risk of adverse reactions.
Preventing or Managing DI | Discuss the use of multiple weak CYP3A4 inhibitors with the patient when prescribing ADDYI.
Strong CYP2C19 Inhibitors
Examples | Proton pump inhibitors, selective serotonin reuptake inhibitors, benzodiazepines, antifungals
Clinical Implications | The concomitant use of ADDYI with strong CYP2C19 inhibitors may increase flibanserin exposure which may increase the risk of hypotension, syncope, and CNS depression.
Preventing or Managing DI | Discuss the use of a strong CYP2C19 inhibitor with the patient when prescribing ADDYI.
CYP3A4 Inducers
Examples | Carbamazepine, phenobarbital, phenytoin, rifabutin, rifampin, rifapetine, St. John's Wort
Clinical Implications | The concomitant use of ADDYI with CYP3A4 inducers substantially decreases flibanserin exposure compared to the use of ADDYI alone.
Preventing or Managing DI | The concomitant use of ADDYI with CYP3A4 inducers is not recommended.
Digoxin or Other P-glycoprotein Substrates
Examples | Digoxin, sirolimus
Clinical Implications | The concomitant use of ADDYI with digoxin, a drug that is transported by P-glycoprotein (P-gp), increases the digoxin concentration [see Clinical Pharmacology (12.3)]. This may lead to digoxin toxicity.
Preventing or Managing DI | Increase monitoring of concentrations of drugs transported by P-gp that have a narrow therapeutic index (e.g., digoxin).

8 USE IN SPECIFIC POPULATIONS

8.1 Pregnancy

Risk Summary
There are no studies of ADDYI in pregnant women to inform whether there is a drug-associated risk in humans. In animals, fetal toxicity only occurred in the presence of significant maternal toxicity including reductions in weight gain and sedation. In pregnant rats and rabbits, adverse reproductive and developmental effects consisted of decreased fetal weight, structural anomalies and increases in fetal loss at exposures greater than 15 times exposures achieved with the recommended human dosage [see Data]. Animal studies cannot rule out the potential for fetal harm.

The estimated background risk of major birth defects and miscarriage for the indicated population is unknown. All pregnancies have a background risk of birth defect, loss, or other adverse outcomes. In the U.S. general population, the estimated background risk of major birth defects and miscarriage in clinically recognized pregnancies is 2% to 4% and 15% to 20%, respectively.

Data
Animal Data
Pregnant rats were administered flibanserin at doses of 0, 20, 80 and 400 mg/kg/day (3, 15 and 41 times clinical exposures at the recommended human dose based on AUC) during organogenesis. The highest dose was associated with significant maternal toxicity as evidenced by severe clinical signs and marked reductions in weight gain during dosing. In the litters of high-dose dams, there were decreased fetal weights, decreased ossification of the forelimbs and increased number of lumbar ribs, and two fetuses with anophthalmia secondary to severe maternal toxicity. The no adverse effect level for embryofetal toxicity was 80 mg/kg/day (15 times clinical exposure based on AUC).

Pregnant rabbits were administered flibanserin at doses of 0, 20, 40 and 80 mg/kg/day (4, 8 and 16 times the clinical exposure at the recommended human dose) during organogenesis. Marked decreases in maternal body weight gain (>75%), abortion and complete litter resorption were observed at 40 and 80 mg/kg/day indicating significant maternal toxicity at these doses. Increases in resorptions and decreased fetal weights were observed at ≥ 40 mg/kg/day. No treatment-related teratogenic effects were observed in fetuses at any dose level. The no adverse effect level for maternal and embryofetal effects was 20 mg/kg/day (3-4 times clinical exposure based on AUC).

Pregnant rats were administered flibanserin at doses of 0, 20, 80 and 200 mg/kg/day (3, 15 and ~ 20 times clinical exposures at the recommended human dose) from day 6 of pregnancy until day 21 of lactation to assess for effects on peri- and postnatal development. The highest dose was associated with clinical signs of toxicity in pregnant and lactating rats. All doses resulted in sedation and decreases in body weight gain during pregnancy. Flibanserin prolonged gestation in some dams in all dose groups and decreased implantations, number of fetuses and fetal weights at 200 mg/kg/day. Dosing dams with 200 mg/kg also decreased pup weight gain and viability during the lactation period and delayed opening of the vagina and auditory canals. Flibanserin had no effects on learning, reflexes, fertility or reproductive capacity of the F1 generation. The no adverse effect level for maternal toxicity and peri/postnatal effects was 20 mg/kg/day [see Nonclinical Toxicology (13.1)].

8.2 Lactation

Risk Summary
Flibanserin is excreted in rat milk. It is unknown whether flibanserin is present in human milk, whether ADDYI has effects on the breastfed infant, or whether ADDYI affects milk production. Because of the potential for serious adverse reactions including sedation in a breastfed infant, ADDYI is not recommended in breastfeeding women.

8.4 Pediatric Use

ADDYI is not indicated for use in pediatric patients.

8.5 Geriatric Use

ADDYI is not indicated for the treatment of HSDD in geriatric patients [see Warnings and Precautions (5.1. 5.2, and 5.4)]. Safety and effectiveness of ADDYI for the treatment of HSDD have not been established in geriatric patients.

8.6 Hepatic Impairment

ADDYI is contraindicated for use in patients with any degree of hepatic impairment. Flibanserin exposure increased 4.5-fold in patients with hepatic impairment, compared to those with normal hepatic function, increasing the risk of hypotension, syncope, and CNS depression [see Boxed Warning, Contraindications (4), Warnings and Precautions (5.5), and Clinical Pharmacology (12.3)].

8.7 CYP2C19 Poor Metabolizers

CYP2C19 poor metabolizers had increased flibanserin exposures compared to CYP2C19 extensive metabolizers. Additionally, syncope occurred in a subject who was a CYP2C19 poor metabolizer [see Adverse Reactions (6.1) and Clinical Pharmacology (12.5)]. Therefore, increase monitoring for adverse reactions (e.g., hypotension) in patients who are CYP2C19 poor metabolizers. The frequencies of poor CYP2C19 metabolizers are approximately 2–5% among Caucasians and Africans and approximately 2–15% among Asians.

10 OVERDOSAGE

Overdosage of ADDYI may cause an increase in the incidence or severity of any of the reported adverse reactions [see Warnings and Precautions (5.3, 5.4) and Adverse Reactions (6.1)]. In the event of overdosage, treatment should address the symptoms and supportive measures, as needed. There is no known specific antidote for flibanserin.

11 DESCRIPTION

The chemical name of flibanserin is 2H-Benzimidazol-2-one, 1,3-dihydro-1-[2-[4-[3-(trifluoromethyl)phenyl]-1-piperazinyl]ethyl]. Its empirical formula is C20H21F3N4O and its molecular weight is 390.41.

The structural formula is:

Flibanserin is a white to off-white powder, insoluble in water, sparingly soluble in methanol, ethanol, acetonitrile and toluene, soluble in acetone, freely soluble in chloroform, and very soluble in methylene chloride.

ADDYI (flibanserin) tablets are for oral administration. Each ADDYI tablet contains 100 mg of flibanserin. Inactive ingredients consist of lactose monohydrate, microcrystalline cellulose, hypromellose, croscarmellose sodium, magnesium stearate, talc, macrogol, and the coloring agents, titanium dioxide and iron oxide.

12 CLINICAL PHARMACOLOGY

12.1 Mechanism of Action

The mechanism of action of ADDYI in the treatment of women less than 65 years of age with acquired, generalized HSDD as characterized by low sexual desire that causes marked distress or interpersonal difficulty (not due a co-existing medical or psychiatric condition, problems within the relationship, or the effects of a medication or other drug substance) is not known.

12.2 Pharmacodynamics

Receptor Binding:
In vitro, flibanserin demonstrated high affinity for the following serotonin (5-hydroxytryptamine or 5-HT) receptors: agonist activity at 5-HT1A and antagonist activity at 5-HT2A. Flibanserin also has moderate antagonist activities at the 5-HT2B, 5-HT2C, and dopamine D4 receptors.

Alcohol Interaction
See Clinical Trials Experience (6.1)

Cardiac Electrophysiology
The effect of ADDYI on the QT interval was evaluated in a randomized, double-blind, placebo- and active- (single dose moxifloxacin) controlled crossover study in 56 healthy men and women. Subjects in the ADDYI groups received either 50 mg twice a day (equivalent to the daily recommended dosage) or 100 mg three times a day (3 times the daily recommended dosage) administered for 5 days. The time frame for electrocardiogram (ECG) measurements covered maximum plasma concentrations of flibanserin and relevant metabolites. In this study, ADDYI did not prolong the QT interval to any clinically relevant extent. The mean increase in heart rate associated with the 100 mg three times a day dose of ADDYI compared to placebo ranged from 1.7 to 3.2 beats per minute.

12.3 Pharmacokinetics

Flibanserin showed dose-proportional pharmacokinetics for Cmax after single oral doses of 100 mg to 250 mg (the recommended and 2.5 times the recommended dosage, respectively) in healthy female subjects. Steady state was achieved after 3 days of dosing. The extent of exposure (AUC0-∞) with once-daily dosing of 100 mg of flibanserin was increased 1.4-fold as compared to a single dose.

Figure 1 Mean + SD Plasma Flibanserin Concentration-Time Profiles in Healthy Female Subjects Following a Single Oral Dose of 100 mg of Flibanserin (Linear Scale)

Absorption
Following oral administration of a single 100 mg dose of flibanserin in healthy premenopausal women (N=8), mean (SD) Cmax was 419 (206) ng/mL and mean (SD) AUC0-inf was 1543 (511) ng*hr/mL. Median (range) time to reach Cmax was 0.75 (0.75 to 4.0) hours. Absolute bioavailability of flibanserin following oral dosing is 33%.

Effect of Food
Food increased the extent of absorption and slowed the rate of absorption of a 50 mg dose of flibanserin (one half the recommended dosage). Low-, moderate-, and high-fat meals increased flibanserin AUC0-inf by 1.18-, 1.43-, and 1.56-fold; increased Cmax by 1.02-, 1.13-, and 1.15-fold; and prolonged median Tmax to 1.5, 0.9, 1.8 hours from 0.8 hours under fasted conditions, respectively.

Distribution
Approximately 98% of flibanserin is bound to human serum proteins, mainly to albumin.

Elimination
Metabolism
Flibanserin is primarily metabolized by CYP3A4 and, to a lesser extent, by CYP2C19. Based on in vitro and/or in vivo data, CYP1A2, CYP2B6, CYP2C8, CYP2C9, and CYP2D6 contribute minimally to the metabolism of flibanserin. After a single oral solution dose of 50 mg ^14C-radiolabeled flibanserin, 44% of the total ^14C-flibanserin related radioactivity was recovered in urine, and 51% was recovered in feces. Flibanserin is extensively metabolized to at least 35 metabolites, most of them occurring in low concentrations in plasma. Two metabolites could be characterized that showed plasma concentrations similar to that achieved with flibanserin: 6,21-dihydroxy-flibanserin-6,21-disulfate and 6-hydroxy-flibanserin-6-sulfate. These two metabolites are inactive.

Excretion
Flibanserin has a mean terminal half-life of approximately 11 hours.

Specific Populations
Hepatic Impairment
Single 50 mg oral doses of flibanserin were administered to 10 patients with mild hepatic impairment (Child-Pugh score of 6 points), 4 patients with moderate hepatic impairment (Child-Pugh score of 8-9 points), and 14 healthy subjects matched by age, weight, and gender. Systemic flibanserin exposure (AUC0-inf) increased 4.5-fold in patients with mild hepatic impairment, compared to subjects with normal hepatic function, and t1/2 was longer (26 hours compared to 10 hours in matching healthy controls). Due to the small number of patients (n=4) with moderate hepatic impairment enrolled in the study, it is not possible to make conclusions about the quantitative effect of moderate hepatic impairment on flibanserin exposure. ADDYI is contraindicated in patients with hepatic impairment [see Warnings and Precautions (5.5)].

Renal Impairment
Single 50 mg oral doses of flibanserin were administered to 7 patients with mild to moderate renal impairment (GFR 30 to 80 mL/min), 9 patients with severe renal impairment (GFR <30 mL/min, not on dialysis), and 16 healthy subjects matched by age, weight, and gender. Flibanserin exposure (AUC0-inf) increased 1.1-fold in patients with mild to moderate renal impairment and 1.2-fold in patients with severe renal impairment, compared to the healthy control subjects.

Race/Ethnicity
A cross-study comparison between healthy Japanese women and Caucasian women with HSDD showed that flibanserin exposure was approximately 1.4-fold higher in Japanese women. When the mean flibanserin exposure in Japanese women was adjusted for weight, the AUCtau,ss in Japanese women was 2246 ng*hr/mL, which is comparable to 2080 ng*hr/mL in Caucasian women. The similarity in weight-adjusted AUCtau,ss suggests that weight, not race, is the factor contributing to the observed difference in flibanserin exposure between Japanese and Caucasian women.

Age
No formal study has been conducted to study the effect of age on flibanserin exposures.

Drug Interaction Studies

Drugs that Increase Flibanserin Exposure
The effects of other drugs on the pharmacokinetics of flibanserin are presented in Table 4 as change relative to flibanserin administered alone (test/reference).

Moderate CYP3A4/Moderate CYP2C9/Strong CYP2C19 Inhibitor (Fluconazole)
In a study of 15 healthy female subjects, a fluconazole 400 mg loading dose followed by 200 mg administered once daily for 5 days increased flibanserin 100 mg single dose exposure (AUC0-inf) 7-fold and Cmax 2.2-fold compared to flibanserin 100 mg alone. Three of 15 subjects (20%) experienced hypotension or syncope from concomitant use of fluconazole and flibanserin; therefore, the study was stopped early [see Warnings and Precautions (5.2), Adverse Reactions (6.1) and Drug Interactions (7)].

Strong CYP3A4 Inhibitor (Ketoconazole)
In a study of 24 healthy female subjects, ketoconazole 400 mg administered once daily for 5 days following a light breakfast increased flibanserin 50 mg single-dose exposure (AUC0-inf) 4.5-fold and Cmax 1.8-fold compared to flibanserin 50 mg alone [see Warnings and Precautions (5.2), Adverse Reactions (6.1) and Drug Interactions (7)].

Strong CYP3A4 Inhibitor (Itraconazole)
In a study of 12 healthy male and female subjects, itraconazole 200 mg administered once daily for 4 days following a loading dose of 400 mg increased flibanserin 50 mg single dose exposure (AUC0-inf) 2.6-fold and Cmax 1.7-fold when flibanserin was given 2 hours after itraconazole on Day 5, compared to exposures with flibanserin 50 mg alone. The 200 mg itraconazole dose does not maximally inhibit the CYP3A4 enzyme [see Drug Interactions (7)].

Moderate CYP3A4 Inhibitor (Grapefruit Juice)
In a study of 26 healthy female subjects, grapefruit juice (240 mL) increased flibanserin 100 mg single dose exposure (AUC0-inf) by 1.4-fold and Cmax 1.1-fold compared to flibanserin 100 mg alone [see Warnings and Precautions (5.2), Adverse Reactions (6.1) and Drug Interactions (7)].

Weak CYP3A4 Inhibitor (Oral Contraceptives)
In a meta-analysis of 17 oral contraceptive users and 91 non-users in Phase 1 studies, the oral contraceptive users had a 1.4-fold higher flibanserin AUC and 1.3‑fold higher Cmax compared to the non-users [see Adverse Reactions (6.1) and Drug Interactions (7)].

Strong CYP2D6 Inhibitor (Paroxetine)
Paroxetine is a strong CYP2D6 inhibitor. In a study of 19 healthy male and female subjects, flibanserin exposure decreased by approximately 4% when flibanserin 50 mg twice daily was given with paroxetine compared to flibanserin alone. Paroxetine was dosed at 20 mg once daily for 3 days followed by 40 mg once daily for 7 days.

Drugs that Decrease Flibanserin Exposure
Strong CYP3A4 Inducer (Rifampin)
In a study of 24 healthy female subjects, rifampin 600 mg given once daily for 7 days prior to administration of 100 mg flibanserin significantly decreased flibanserin exposure by 95% [see Drug Interactions (7)].

Moderate CYP3A4 Inducer (Etravirine)
Steady state etravirine, a moderate CYP3A4 inducer, decreased flibanserin exposures by approximately 21% [see Drug Interactions (7)].

Table 4 Drugs That Increase Flibanserin Exposure
Coadministered Drug(s) and Dose(s) | Dose of ADDYI | n | Geometric Mean Ratio (90% Confidence Interval) of Pharmacokinetic Parameters of Flibanserin with/without Coadministered Drug No Effect =1.00
Coadministered Drug(s) and Dose(s) | Dose of ADDYI | n | Cmax | AUC0-inf
Fluconazole 200 mg | 100 mg | 15 | 2.2 (1.8 – 2.8) | 7.0 (6.0 – 8.2)
Ketoconazole 400 mg | 50 mg | 24 | 1.8 (1.7 – 2.1) | 4.5 (4.0 – 5.1)
Itraconazole 200 mg [itraconazole dose was not optimal for maximal inhibition of CYP3A4 enzyme.] | 50 mg | 12 | 1.7 (1.4 – 2.0) | 2.6 (2.1 – 3.0)
Oral Contraceptives | 50 mg | 39 | 1.3 (1.1 – 1.6) | 1.4 (1.2 – 1.7)
Paroxetine 40 mg | 50 mg twice daily | 19 | 1.0 (0.9 – 1.2) | 1.0 (0.9 – 1.0)

Effects of Flibanserin on Other Drugs
The effects of flibanserin on the pharmacokinetics of other drugs are presented in Table 5 as change relative to the other drug administered alone (test/reference).

Digoxin and P-glycoprotein Substrates
A single center, open-label, randomized, two-way crossover study in 24 healthy men and women evaluated the effect of flibanserin on the pharmacokinetics of digoxin. Flibanserin 100 mg was administered once daily over 5 days followed by a single dose of 0.5 mg digoxin, a P-gp substrate. Flibanserin increased digoxin AUC0-inf by 2.0-fold and Cmax by 1.5-fold, compared to digoxin alone [see Drug Interactions (7)].

Drugs Metabolized by CYP3A4 (Simvastatin)
An open-label, randomized, crossover study in 12 healthy men and women evaluated the effect of flibanserin 50 mg twice daily for 4 days on the pharmacokinetics of simvastatin 40 mg once daily. Flibanserin increased the AUC0-inf of simvastatin, a substrate of CYP3A4, 1.3‑fold and Cmax by 1.2-fold. Flibanserin co-administered with simvastatin increased simvastatin acid AUC0-inf by 1.5-fold and Cmax by 1.4-fold.

Oral Contraceptives
A study in 24 healthy women evaluated the effect of 100 mg flibanserin once daily for 2 weeks on the pharmacokinetics of a single-dose of ethinyl estradiol (EE) 30 mcg/levonorgestrel (LNG) 150 mcg. Flibanserin increased the EE AUC0-inf by 1.09-fold and the EE Cmax by 1.1-fold. Flibanserin decreased the LNG AUC0-inf by 1.06-fold and did not change the LNG Cmax. [see Adverse Events (6.1), Drug Interactions (7)].

Drugs Metabolized by CYP2B6 (Bupropion)
An open-label, randomized, two-period crossover study in 28 healthy women evaluated the effect of flibanserin on the pharmacokinetics of bupropion. Flibanserin 50 mg twice daily was administered for 2 days followed by 100 mg once daily for 13 days. Bupropion 150 mg twice daily was given for 8 days beginning on Day 6 of flibanserin treatment. Flibanserin did not change bupropion AUCt,ss (1.0-fold change) and Cmax (1.0-fold change) but hydroxybupropion AUCt,ss decreased by 9% and Cmax by 11%.

Table 5 Effects of Flibanserin on Exposure of Other Drugs
Coadministered Drug(s) and Dose(s) | Dose of ADDYI | n | Geometric Mean Ratio (90% Confidence Interval) of Pharmacokinetic Parameters of Coadministered Drug with/without Flibanserin No Effect =1.00
Coadministered Drug(s) and Dose(s) | Dose of ADDYI | n | Cmax | AUC0-inf
Simvastatin 40 mg | 50 mg twice daily | 12 | 1.7 (1.4 – 2.0) | 2.6 (2.1 – 3.1)
Digoxin 0.5 mg | 100 mg | 24 | 1.5 (1.3 – 1.6) | 2.0 (1.5 – 2.5)
Ethinyl estradiol 30 mcg/ Levonorgestrel 150 mcg | 100 mg | 24 | 1.1 (1.0 – 1.1) 1.0 (0.9 – 1.0) | 1.1 (1.0 – 1.2) 1.0 (0.9 – 1.1)
Bupropion 150 mg | 100 mg | 28 | 1.0 (0.9 – 1.1) | 1.0 (1.0 – 1.1)

12.5 Pharmacogenomics

Patients who are poor metabolizers of CYP2D6, CYP2C9 or CYP2C19 are deficient in CYP2D6, CYP2C9 or CYP2C19 enzyme activity, respectively. Extensive metabolizers have normal functioning CYP enzymes.

CYP2C19 Poor Metabolizers
A study comparing flibanserin exposure in CYP2C19 poor metabolizers to CYP2C19 extensive metabolizers was conducted in lieu of a drug interaction study with ADDYI and a strong CYP2C19 inhibitor. In 9 women who were poor metabolizers of CYP2C19, Cmax and AUC0-inf of flibanserin 100 mg once daily increased 1.5-fold (1.1-2.1) and 1.3-fold (0.9-2.1), compared to exposures among 8 extensive metabolizers of CYP2C19. Flibanserin half-life was increased from 11.1 hours in the extensive metabolizers of CYP2C19 to 13.5 hours in the poor metabolizers of CYP2C19 [see Adverse Reactions (6.1) and Use in Specific Populations (8.7)].

The frequencies of poor metabolizers of CYP2C19 are approximately 2–5% among Caucasians and Africans and approximately 2–15% among Asians.

CYP2D6 Poor Metabolizers
A study comparing flibanserin exposure in CYP2D6 poor metabolizers to CYP2D6 extensive metabolizers was conducted in addition to a drug interaction study with paroxetine, a strong CYP2D6 inhibitor. In 12 poor metabolizers of CYP2D6, steady state Cmax and AUC of flibanserin 50 mg twice daily was decreased by 4% and increased by 18%, respectively, compared to exposures among 19 extensive metabolizers, intermediate metabolizers and ultra rapid metabolizers of CYP2D6.

CYP2C9 Poor Metabolizers
A study comparing flibanserin exposure in CYP2C9 poor metabolizers to CYP2C9 extensive metabolizers was conducted in lieu of a drug interaction study with ADDYI and a strong CYP2C9 inhibitor. In 8 women who were poor metabolizers of CYP2C9, Cmax and AUC0-inf of flibanserin 100 mg once daily decreased 23% and 18%, compared to exposures among 8 extensive metabolizers of CYP2C9.

13 NONCLINICAL TOXICOLOGY

13.1 Carcinogenesis, Mutagenesis, Impairment of Fertility

Carcinogenesis
A two-year carcinogenicity study was conducted in CD-1 mice with dietary administration of 0, 10, 80, 200 and 1000/1200 mg/kg/day of flibanserin. Statistically significant increases in combined mammary tumors (adenoacanthomas and adenocarcinomas) were observed in female mice administered flibanserin at doses of 200 and 1200 mg/kg/day (exposures, based on AUC, were 3 and 10 times the clinical exposures at the recommended clinical dose). No increases in mammary tumors were observed in male mice. Statistically significant increases were also seen for combined hepatocellular adenomas/carcinomas in female mice treated with flibanserin 1200 mg/kg/day and for hepatocellular carcinomas in male mice treated with flibanserin 1000 mg/kg/day (exposures, based on AUC, were 8 times the clinical exposure at the recommended clinical dose).

There were no significant increases in tumor incidence in a two year carcinogenicity study conducted in Wistar rats with dietary administration of 0, 10, 30 and 100 mg/kg/day flibanserin (up to 5-8 times human exposure at the recommended clinical dose).

Mutagenesis
Flibanserin was negative for mutagenesis in vitro in Salmonella typhimurium (Ames test) and in Chinese hamster ovary cells. Flibanserin was positive for chromosomal aberrations in cultured human lymphocytes but negative for chromosomal aberrations in vivo in the rat bone marrow micronucleus assay and negative for DNA damage in rat liver in the Comet assay.

Impairment of Fertility
Female and male rats were administered flibanserin 14 and 28 days before mating, respectively, to assess for potential effects on fertility and early reproductive performance. Flibanserin slightly increased the duration of the estrus cycle but had no adverse effects on fertility or early embryonic development at doses up to 200 mg/kg/day (~20 times human exposure at the recommended clinical dose).

14 CLINICAL STUDIES

14.1 Trials in Premenopausal Patients with HSDD

The efficacy of ADDYI for the treatment of acquired, generalized HSDD in premenopausal women [see Indications and Usage (1)] was established in three 24-week, randomized, double-blind, placebo-controlled trials (Study 1, NCT00360529; Study 2, NCT00360555; and Study 3, NCT00996164). The clinical trials enrolled premenopausal women with acquired, generalized HSDD of at least 6 months duration as evidenced by low sexual desire that caused marked distress or interpersonal difficulty and was not due to: a co-existing medical or psychiatric condition, problems with the relationship, or the effects of a medication or other drug substance. Acquired HSDD was defined as HSDD that developed in patients who previously had no problems with sexual desire. Generalized HSDD was defined as HSDD that was not limited to certain types of stimulation, situations or partners.

The patients were treated with ADDYI 100 mg once daily at bedtime (n = 1187) or placebo (n = 1188). Most of the trial participants were Caucasian (88.6%); the remainder were Black (9.6%) and Asian (1.5%). The mean age of study participants was 36 years old (range 19 to 55 years old); the mean duration in the monogamous, heterosexual relationship was 11 years, and the mean duration of HSDD was approximately 5 years. The completion rate across these three trials was 69% and 78% for the ADDYI and placebo groups, respectively.

These trials each had two co-primary efficacy endpoints, one for satisfying sexual events (SSEs) and the other for sexual desire:

- The change from baseline to Week 24 in the number of monthly SSEs (i.e., sexual intercourse, oral sex, masturbation, or genital stimulation by the partner). The SSEs were based on patient responses to the following questions: “Did you have a sexual event?” and “Was the sex satisfying for you?”
- Studies 1 and 2 had a different sexual desire endpoint than Studies 3:
  - In Studies 1 and 2, the sexual desire co-primary endpoint was the change from baseline to Week 24 in the calculated monthly sexual desire score and was based on patient responses to the question: “Indicate your most intense level of sexual desire.” Every day, patients rated their sexual desire level from 0 (no desire) to 3 (strong desire) and recorded their response in an electronic Diary (eDiary). These responses were summed over a 28-day period to yield the calculated monthly sexual desire score, which ranged from 0 to 84.
  - In Study 3, the desire domain of the Female Sexual Function Index (FSFI Desire) was the sexual desire co-primary endpoint. The desire domain of the FSFI has two questions. The first question asks patients “Over the past 4 weeks, how often did you feel sexual desire or interest?”, with responses ranging from 1 (almost never or never) to 5 (almost always or always). The second question asks patients “Over the past 4 weeks, how would you rate your level (degree) of sexual desire or interest?”, with responses ranging from 1 (very low or none at all) to 5 (very high). The FSFI Desire score was calculated by adding the patient’s responses to these two questions then multiplying that sum by 0.6. The FSFI Desire domain score ranged from 1.2 to 6.

The desire domain of the Female Sexual Function Index (FSFI Desire) was also used as a secondary endpoint in Studies 1 and 2.

The three trials had a secondary endpoint that measured bother (a component of distress) related to sexual desire using Question 13 of the Female Sexual Distress Scale-Revised (FSDS-R). This question asks “How often did you feel: Bothered by low sexual desire?” Patients assessed their sexual distress over a 7-day recall period and responded on a scale of 0 (never) to 4 (always).

The efficacy results from Studies 1, 2, and 3 are summarized in Table 6. In the three trials, ADDYI resulted in statistically significant improvement compared to placebo in the change from baseline in monthly SSEs at Week 24. In Study 1 and 2, there were no statistically significant differences between ADDYI and placebo for the eDiary sexual desire endpoint (change in baseline to Week 24). In contrast, in Study 3 there was statistically significant improvement in the change from baseline to Week 24 in sexual desire (using the FSFI Desire Domain) with ADDYI compared to placebo. The FSFI Desire Domain findings were consistent across all three trials as were the findings for the secondary endpoint that assessed distress using Question 13 of the FSDS-R.

Table 6 Efficacy Results in Premenopausal HSDD Patients in Studies 1, 2, and 3
 | Study 1 |  | Study 2 [Excludes subjects from two study sites that had data integrity issues] |  | Study 3
 | ADDYI | Placebo | ADDYI | Placebo | ADDYI | Placebo
Full Analysis Set | n=280 | n=290 | n=365 | n=372 | n=532 | n=536
Number of satisfying sexual events (per 28 days)
Baseline (Mean) | 3.0 | 2.7 | 2.6 | 2.7 | 2.5 | 2.7
Change from baseline (Mean) | 1.6 | 0.8 | 1.8 | 1.1 | 2.5 | 1.5
Treatment diff. (95% CI) | 0.9 (0.3, 1.4) | 0.0 | 0.6 (-0.03, 1.2) | 0.5 | 1.0 (0.4, 1.5) | 0.5
Change from baseline (Median) | 1.0 |  | 1.0 |  | 1.0
Median treatment difference | 1.0 |  | 0.5 |  | 0.5
p-value vs placebo | p<0.01 |  | p<0.01 |  | p<0.0001
e-Diary Desire
Baseline (Mean) | 12.9 | 11.8 | 12.1 | 10.2 | Not Used | Not Used
Change from baseline at Week 24 (Mean) | 9.1 | 6.9 | 8.3 | 6.7
Treatment diff. (95% CI) | 2.3 (-0.1, 4.7) |  | 1.7 (-0.5, 4.0)
p-value vs placebo | NS |  | NS
FSFI Desire
Baseline (Mean) | 1.9 | 1.9 | 1.8 | 1.8 | 1.9 | 1.9
Change from baseline at Week 24 (Mean) | 0.9 | 0.5 | 0.9 | 0.5 | 1.0 | 0.7
Treatment diff. (95% CI) | 0.4 (0.2, 0.5) |  | 0.3 (0.2, 0.5) |  | 0.3 (0.2, 0.4)
p-value vs placebo | N/A [p-value not reported for secondary endpoints because the trial failed on the eDiary Desire co-primary efficacy endpoint] |  | N/A |  | p<0.0001
FSDS-R Question 13 [A decrease in score represents improvement]
Baseline (Mean) | 3.2 | 3.2 | 3.2 | 3.2 | 3.4 | 3.4
Change from baseline at Week 24 (Mean) | -0.8 | -0.5 | -0.8 | -0.5 | -1.0 | -0.7
Treatment diff. (95% CI) | -0.4 (-0.5, -0.2) |  | -0.3 (-0.4, -0.1) |  | -0.3 (-0.4, -0.1)
p-value vs placebo | N/A |  | N/A |  | p=0.0001
CI = Confidence Interval; NS = not statistically significant; N/A = not applicable
Shaded cells show the results for the co-primary efficacy endpoints for each trial.
e-Diary desire was evaluated as a co-primary endpoint in Studies 1 and 2; FSFI desire was evaluated as a co-primary endpoint in Study 3.
The efficacy results are based on the full analysis set comprised of all randomized patients who took at least one dose of study medication and had at least one on-treatment efficacy assessment. Missing values were imputed using last-observation-carried-forward.
The unadjusted means are presented for the baseline values.
For satisfying sexual events, p-values are based on the Wilcoxon rank sum test stratified by pooled center. Median change from baseline is shown because the data are not normally distributed.
For FSFI-desire, e-Diary desire, and FSDS-R Question 13, reported p-values are based on an ANCOVA model using baseline as a covariate with treatment and pooled center as main effect terms. For the change from baseline, the adjusted least squares mean (standard error) are presented.

Exploratory analyses were conducted to assess whether the treatment effects varied depending on baseline number of SSEs, FSFI desire score, and FSDS-R Question 13 distress score. No notable differences were identified among these subgroups.

Supportive analyses were conducted to help interpret the clinical meaningfulness of the observed treatment effects. These analyses defined responders for each efficacy endpoint by anchoring change from baseline to end of treatment with the Patient's Global Impression of Improvement (PGI‑I). The first analysis considered responders to be those who reported being “much improved” or “very much improved.” In this analysis, the absolute difference in the percentage of responders with ADDYI and the percentage of responders with placebo across the three trials in premenopausal women was 8-9% for SSEs (29-39% for ADDYI; 21-31% for placebo), 10-13% for FSFI desire domain (43-48% for ADDYI; 31-38% for placebo), and 7-13% for FSDS-R Question 13 (21-34% for ADDYI; 14-25% for placebo). The second analysis considered responders to be those who reported being at least "minimally improved". The absolute difference in the percentage of responders with ADDYI and the percentage of responders with placebo across the three trials in premenopausal women was 10-15% for SSEs (44-48% for ADDYI; 33-36% for placebo), 12-13% for FSFI desire domain (43-51% for ADDYI; 31-39% for placebo), and 9-12% for FSDS-R Question 13 (50-60% for ADDYI; 41-48% for placebo).

14.2 Trials in Postmenopausal Patients with HSDD (< 65 Years of Age)

The efficacy of ADDYI for the treatment of acquired, generalized HSDD in naturally postmenopausal women less than 65 years of age [see Indications and Usage (1)] was established in a single 24-week, randomized, double-blind, placebo-controlled trial (Study 6, NCT00996372). The trial included postmenopausal women with acquired, generalized HSDD of at least 6 months duration.

In Study 6, 447 postmenopausal patients less than 65 years of age received ADDYI 100 mg once daily at bedtime and 455 received placebo. Most of the trial participants less than 65 years of age were White (92%); the remainder were Black (7%) and Asian (1%). The mean age of study participants less than 65 years of age was 55 years (range 39 to 64 years); the mean duration in the monogamous, heterosexual relationship was 21 years, and the mean duration of HSDD was approximately 5 years. The study completion rate for the ADDYI and placebo groups less than 65 years of age was 79% and 83%, respectively. In this trial, postmenopausal patients with significant comorbidities such as uncontrolled hypertension, uncontrolled diabetes mellitus (Hgb A1C > 7%), cardiovascular disease, uncorrected thyroid disorders, psychiatric disorders, etc., were excluded.

The trial had two co-primary efficacy endpoints - one for SSEs counts and one for desire domain of the Female Sexual Function Index (FSFI Desire) (similar to Study 3) - and a secondary endpoint that measured bother (a component of distress) related to sexual desire using Question 13 FSDS-R. These endpoints are defined in Section 14.1.

The efficacy results for patients less than 65 years of age from Study 6 are summarized in Table 7. ADDYI resulted in statistically significant improvement compared to placebo in the co-primary and secondary endpoints.

Table 7 Efficacy Results in Postmenopausal HSDD Patients in Study 6 (<65 Years of Age)
Full Analysis Set <65 years of age | ADDYI n=430 | Placebo n=451
Number of satisfying sexual events (count) per 28 days
Baseline (Mean); Change from baseline at Week 24 (Mean); Treatment difference (95% CI) | 2.0; 0.9; 0.4 (-0.0, 0.8); p < 0.025 | 2.0; 0.6
FSFI Desire
Baseline (Mean); Change from baseline at Week 24 (Mean); Treatment difference (95% CI) | 1.8; 0.7; 0.3 (0.2, 0.5); p < 0.0001 | 1.8; 0.4
FSDS-R Question 13 [A decreased in scope represents improvement]
Baseline (Mean); Change from baseline at Week 24 (Mean); Treatment difference (95% CI) | 3.3; -0.8; -0.2 (-0.4, -0.1); p < 0.01 | 3.3; -0.6
CI = Confidence Interval
The efficacy results are based on the full analysis set <65 years of age comprised of all randomized patients <65 years of age who took at least one dose of study medication and had at least one post-baseline efficacy assessment. Missing values were imputed using last-observation-carried-forward.
For satisfying sexual events, p-values are based on the Wilcoxon rank sum test. For FSFI-desire and FSDS-R Question 13, reported p-values are based on an ANCOVA model using baseline as a covariate with treatment and pooled center as main effect terms.
The unadjusted means are presented for the baseline values. For the change from baseline, the adjusted least squares means are presented.

14.3 Effects on Driving

In a randomized, placebo-controlled, 4-way crossover study in 83 healthy premenopausal female subjects, no adverse effect was detected on measures of driving performance itself or psychomotor performance thought to be important for driving performance when assessed 9 hours following single and multiple doses of ADDYI 100 mg once daily at bedtime or single doses of ADDYI 200 mg at bedtime (two times the maximum recommended dosage) [see Warnings and Precautions (5.3)].

The effect of ADDYI on driving performance in postmenopausal women was not evaluated.

16 HOW SUPPLIED/STORAGE AND HANDLING

ADDYI is available as a 100 mg oval, pink, film-coated tablet debossed on one side with “f100” and blank on the other side. Available in bottles of 30 tablets. (NDC 58604-214-30)

Storage
Store at 25°C (77°F); excursions permitted to 15°-30°C (59°-86°F) [see USP controlled room temperature].

17 PATIENT COUNSELING INFORMATION

Advise the patient to read the FDA-approved patient labeling (Medication Guide).

Hypotension and Syncope

Inform patients that ADDYI can cause severe hypotension and syncope, particularly when taken close in time with alcoholic drinks or with moderate or strong CYP3A4 inhibitors.

- Counsel patients to wait at least two hours after consuming one or two standard alcoholic drinks before taking ADDYI at bedtime or to skip their ADDYI dose if they have consumed 3 or more standard alcoholic drinks that evening.
  After taking ADDYI at bedtime, advise patients to not use alcohol until the following day.
- Advise patients that moderate or strong CYP3A4 inhibitors are contraindicated with ADDYI and to ask patients to report the use of a new prescription or non-prescription medication or other products that contain CYP3A4 inhibitors (e.g., grapefruit juice, St. John’s Wort).
- Advise patients who experience pre-syncope or lightheadedness to lie down and to call for help if symptoms persist [see Contraindications (4), Warnings and Precautions (5.1, 5.2)].

CNS Depression
Advise patients that ADDYI can cause CNS depression, such as somnolence and sedation, and that the risk is increased with other CNS depressants and with certain drug interactions (e.g., hypnotics, benzodiazepines, opioids). The risk is also increased if ADDYI is taken during waking hours. Advise patients to avoid activities requiring full alertness (e.g., driving or operating machinery) until at least 6 hours after the ADDYI dose and until they know how ADDYI affects them [see Warnings and Precautions (5.3)].

Nursing Mothers
Advise patients not to breastfeed if they are taking ADDYI [see Use in Specific Populations (8.2)].

Bedtime Dosing
Advise patients to take only one tablet at bedtime and not to take ADDYI at any other time of day [see Dosage and Administration (2)].

Distributed by:
Sprout Pharmaceuticals, Inc.
Raleigh, NC 27609 USA
Product and trademark licensed from:
Sprout Pharmaceuticals, Inc.

Copyright 2025 Sprout Pharmaceuticals, Inc.
All rights reserved

ADDYI tablets are covered by U.S. Patents Nos. 7,151,103; 7,420,057; 7,183,410; 8,227,471; 9,468,639; and 9,782,403.

IT5046AJ0909
10005639/01

MEDICATION GUIDE

ADDYI® (add-ee)
(flibanserin)
tablets, for oral use

Read this Medication Guide before you start taking ADDYI® and each time you get a refill. There may be new information. This information does not take the place of talking to your doctor.

What is the most important information I should know about ADDYI?
Your risk of severe low blood pressure and fainting (loss of consciousness) is increased:

- if you drink alcohol close to the time you take your ADDYI dose,
- if you take ADDYI with certain medicines, or
- if you have liver problems and you take ADDYI.

To lower your risk of low blood pressure and fainting (loss of consciousness):

- Do not drink alcohol close to the time you take your ADDYI dose.

- After taking ADDYI at bedtime do not drink alcohol until the following day.
Examples of 1 standard alcoholic drink include:
  1. one 12-ounce regular beer
  2. 5 ounces of wine
  3. 1.5 ounces of distilled spirits or shot
- Tell your doctor about other medicines you take. Do not take or start taking any prescription or over-the-counter medicines, or herbal supplements without first talking to your doctor. Your doctor will tell you if it is safe to take other medicines or herbal supplements while you are taking ADDYI.
- Do not take ADDYI if you have liver problems.

If you take ADDYI and you feel lightheaded or dizzy, lie down right away. Get emergency medical help or ask someone to get emergency medical help for you if the symptoms do not go away or if you feel like you could faint (lose consciousness). If you faint (lose consciousness), tell your doctor as soon as you can.

What is ADDYI?

ADDYI is a prescription medicine used to treat hypoactive (low) sexual desire disorder (HSDD) in women <65 years of age who have not had problems with low sexual desire in the past, and who have low sexual desire no matter the type of sexual activity, the situation, or the sexual partner. Women with HSDD have low sexual desire that is troubling to them. Their low sexual desire is not due to:

- a medical or mental health problem
- problem in the relationship
- medicine or other drug use

ADDYI is not for use in men.
ADDYI is not for use to improve sexual performance.
ADDYI is not for use in Children.

Who should not take ADDYI?
Do not take ADDYI if you:

- take certain other medicines. Taking ADDYI with certain other medicines can increase the amount of ADDYI in your blood and cause severe low blood pressure, fainting (loss of consciousness), and sleepiness.
  Do not take ADDYI if you are taking any of the following medicines:
  - certain medicines used to treat HIV-1 infection, such as:
    - amprenavir
    - atazanavir (REYATAZ®)
    - fosamprenavir (LEXIVA)
    - ritonavir (NORVIR)
    - saquinavir (INVIRASE®)
    - nelfinavir (VIRACEPT®)
    - indinavir (CRIXIVAN®)
  - certain medicines that you take by mouth used to treat fungal infections, such as:
    - fluconazole (DIFLUCAN®)
    - ketoconazole
    - itraconazole (ONMEL, SPORANOX®)
    - posaconazole (NOXAFIL®)
  - certain antibiotics, including:
    - ciprofloxacin (CIPRO, CIPRO XR)
    - erythromycin (ERY-TAB®,ERYC®,PCE®)
    - telithromycin (KETEK®)
    - clarithromycin (BIAXIN®)
  - certain medicines used to treat Hepatitis C infection, such as:
    - boceprevir (VICTRELIS®)
    - telaprevir
  - certain medicines used to treat high blood pressure, chest pain (angina), or other heart problems, such as:
    - diltiazem (CARDIZEM®,CARDIZEM CD®, CARDIZEM LA®, CARTIA XT, DILT CD, DILTZAC, TAZTIA XT, Tiazac®)
    - verapamil (CALAN®, CALAN® SR, COVERA-HS®, Verelan®, Verelan PM)
    - conivaptan (Vaprisol®)
  - nefazodone: a medicine used to treat depression
    Ask your doctor or pharmacist if you are not sure if you take any of the medicines listed above.
    These are examples of the medicines that you should not take if you are taking ADDYI. Tell your doctor about all of the medicines you take before you start taking ADDYI.
- have liver problems

What should I tell my doctor before taking ADDYI?
Before you take ADDYI, tell your doctor about all of your medical conditions, including if you:

- drink alcohol, use drugs or have a history of alcohol or drug abuse
- have ever had depression or other mental health problems
- have low blood pressure or a medical condition that can cause low blood pressure
- are pregnant or plan to become pregnant. It is not known if ADDYI will harm your unborn baby.
- are breastfeeding or plan to breastfeed. It is not known if ADDYI passes into your breast milk. You and your doctor should decide if you will take ADDYI or breastfeed. You should not do both.

Tell your doctor about all of the medicines you take, including prescription and over-the-counter medicines, vitamins, and herbal supplements. ADDYI can affect the way other medicines work, and other medicines can affect the way ADDYI works, and can cause serious side effects.
Know the medicines and herbal supplements you take. Keep a list of them to show your doctor or pharmacist each time you get a new medicine.

How should I take ADDYI?

- Take ADDYI exactly as your doctor tells you to take it.
- Take 1 ADDYI tablet one time a day at bedtime.
- Take ADDYI only at bedtime. Taking ADDYI at a time other than bedtime can increase your risk of low blood pressure, fainting (loss of consciousness), accidental injury, and sleepiness.
- If you drink alcohol, see “What is the most important information I should know about ADDYI?”
- If you miss a dose of ADDYI, skip your missed dose. Take your next dose at bedtime the next day. Do not take ADDYI the next morning or double your next dose. If you take too much ADDYI, call your doctor.
- Tell your doctor if your symptoms of HSDD have not improved after you have taken ADDYI for 8 weeks.

What should I avoid while taking ADDYI?

- Do not drink alcohol close to the time you take your ADDYI dose because this increases your risk of severe low blood pressure and fainting (loss of consciousness).
- Do not drive, operate machinery, or do things that require clear thinking until at least 6 hours after you take ADDYI and until you know how ADDYI affects you.
- Do not drink grapefruit juice if you take ADDYI. Drinking grapefruit juice during your treatment with ADDYI increases your risk of severe low blood pressure and fainting (loss of consciousness).
- You should not take the herbal supplements St. John’s Wort, ginkgo, or resveratrol or certain over-the-counter medicines such as cimetidine until you talk to your doctor. Taking ADDYI with these herbal supplements and over-the-counter medicine may increase your risk of low blood pressure, fainting (loss of consciousness), and sleepiness.

What are the possible side effects of ADDYI?
ADDYI can cause serious side effects, including:

- See “What is the most important information I should know about ADDYI?”
- Sleepiness is a common side effect of ADDYI and can be serious. Taking ADDYI can increase your risk of sleepiness if taken during waking hours, if you drink alcohol, or take certain medicines or herbal supplements.
- Low blood pressure and fainting (loss of consciousness) can happen when you take ADDYI even if you do not drink alcohol or take other medicines or herbal supplements. Your risk of low blood pressure and fainting (loss of consciousness) is increased if ADDYI is taken during waking hours, if you drink alcohol within 2 hours of taking ADDYI, or if you take certain medicines or herbal supplements.

The most common side effects of ADDYI include:

- dizziness
- nausea
- tiredness
- difficulty falling asleep or staying asleep
- dry mouth

These are not all of the possible side effects of ADDYI.
Call your doctor for medical advice about side effects. You may report side effects to FDA at 1-800-FDA-1088.

How should I store ADDYI?

- Store ADDYI at room temperature between 68°F to 77°F (20°C to 25°C).

Keep ADDYI and all medicines out of the reach of children.

General information about the safe and effective use of ADDYI
Medicines are sometimes prescribed for purposes other than those listed in a Medication Guide. Do not use ADDYI for a condition for which it was not prescribed. Do not give ADDYI to other people, even if they have the same symptoms that you have. It may harm them. You can ask your doctor or pharmacist for information about ADDYI that is written for health professionals.

What are the ingredients in ADDYI?
Active ingredient: flibanserin
Inactive ingredients: lactose monohydrate, microcrystalline cellulose, hypromellose, croscarmellose sodium, magnesium stearate, talc, macrogol, and the coloring agents, titanium dioxide and iron oxide.

Sprout Pharmaceuticals, Inc. Raleigh, NC 27609 USA

Copyright © 2025 Sprout Pharmaceuticals, Inc.

For more information go to www.ADDYI.com or call 1‑844-PINK-PILL (1-844-746-5745).

This Medication Guide has been approved by the U.S. Food and Drug Administration.

Revised: 12/2025

PRINCIPAL DISPLAY PANEL - Carton Label

Rx only
NDC 58604-214-30
addyi®
(flibanserin) tablets
100 mg
Attention Pharmacist: Dispense in original packaging. Dispense the accompanying Medication Guide to each patient.
30 Tablets

PRINCIPAL DISPLAY PANEL - Bottle Label

Rx only
NDC 58604-214-30
addyi®
(flibanserin) tablets
100 mg
Attention Pharmacist: Dispense in original packaging. Dispense the accompanying Medication Guide to each patient.
30 Tablets